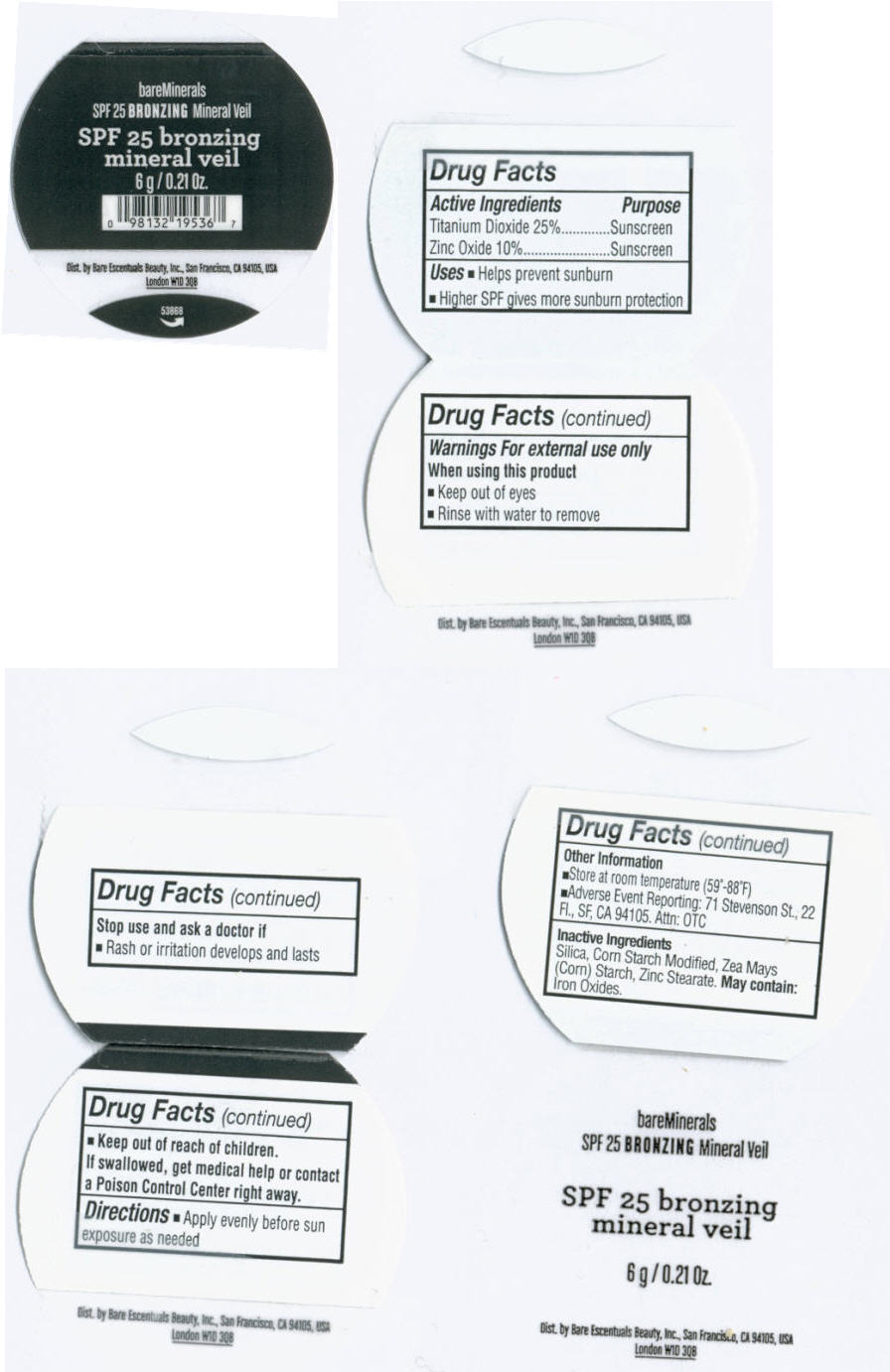 DRUG LABEL: BareMinerals 
NDC: 98132-161 | Form: POWDER
Manufacturer: Bare Escentuals Beauty Inc.
Category: otc | Type: HUMAN OTC DRUG LABEL
Date: 20110726

ACTIVE INGREDIENTS: Titanium Dioxide 25 g/100 g; Zinc Oxide 10 g/100 g
INACTIVE INGREDIENTS: Silicon Dioxide; Starch, Corn; Zinc Stearate; Magnesium Stearate; Ferric Oxide Red

bareMinerals
Bronzing Mineral Veil

Drug Facts

ACTIVE INGREDIENT

Active Ingredients | Purpose
Titanium Dioxide 25% | Sunscreen
Zinc Oxide 10% | Sunscreen

Uses

- Helps prevent sunburn
- Higher SPF gives more sunburn protection

Warnings

For external use only

When using this product

- Keep out of eyes
- Rinse with water to remove

Stop use and ask a doctor if

- Rash or irritation develops and lasts

- Keep out of reach of children.

If swallowed, get medical help or contact a Poison Control Center right away.

Directions

- Apply evenly before sun exposure as needed

Other Information

- Store at room temperature (59°-88°F)
- Adverse Even Reporting: 71 Stevenson St., 22 Fl., SF, CA 94105. Attn: OTC

Inactive Ingredients

Silica, Corn Starch Modified, Zea Mays (Corn) Starch, Zinc Stearate. May contain: Iron Oxides.

Dist. by Bare Escentuals Beauty, Inc., San Francisco, CA 94105, USA

PRINCIPAL DISPLAY PANEL - 6 g Jar

bareMinerals
SPF 25 BRONZING Mineral Veil

SPF 25 bronzing
mineral veil

6 g / 0.21 Oz.